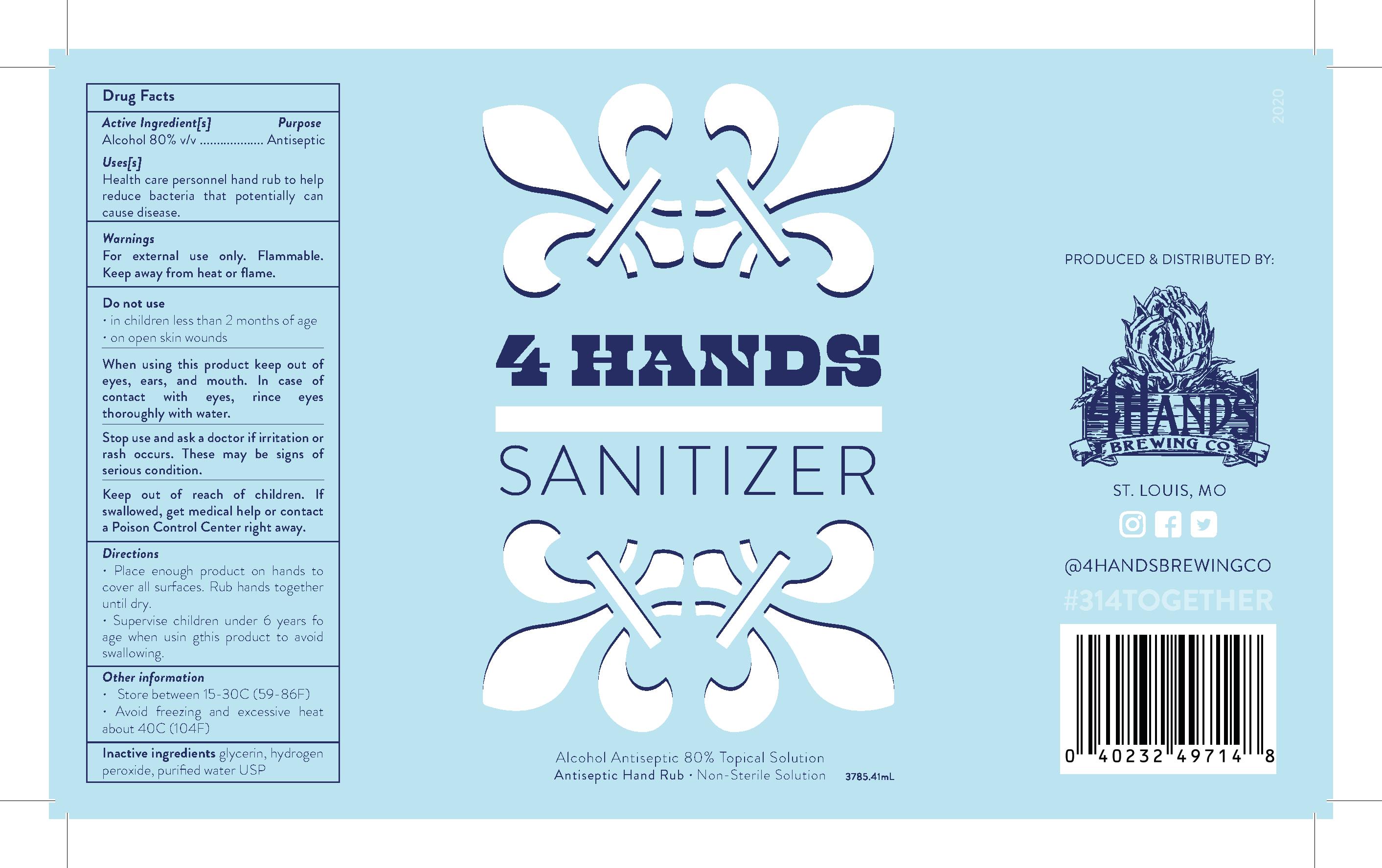 DRUG LABEL: 4 Hands Sanitizer
NDC: 73951-0001 | Form: SOLUTION
Manufacturer: 4 Hands Brewing Company, LLC
Category: otc | Type: HUMAN OTC DRUG LABEL
Date: 20200414

ACTIVE INGREDIENTS: ALCOHOL 80 mL/100 mL
INACTIVE INGREDIENTS: GLYCERIN; WATER; HYDROGEN PEROXIDE

4 Hands Sanitizer

This is a hand sanitizer manufactured according to the Temporary Policy for Preparation of Certain Alcohol-Based Hand Sanitizer Products During the Public Health Emergency.

The hand sanitizer is manufactured using only the following United States Pharmacopoeia (USP) grade ingredients in the preparation of the product (percentag
a. Alcohol (ethanol) (USP or Food Chemical Codex (FCC) grade) (80%, volume/volume (v/v)) in an aqueous solution denatured according to Alcohol and Toba
b. Glycerol (1.45% v/v).
c. Hydrogen peroxide (0.125% v/v).
d. Sterile distilled water or boiled cold water.
The firm does not add other active or inactive ingredients. Different or additional ingredients may impact the quality and potency of the product.

Active Ingredient

Alcohol 80% v/v. Purpose: Antiseptic

Purpose

Antiseptic, Hand Sanitizer

Warnings

For external use only. Flammable. Keep away from heat or flame.

Do Not Use

- in children less than 2 months of age
- on open skin wounds

When using this product keep out of eyes, ears, and mouth. In case of contact with eyes, rinse eyes thoroughly with water.

Stop use and ask a doctor if irritation or rash occurs. These may be signs of a serious condition.

Keep out of reach of children. If swallowed, get medical help or contact a Poison Control Center right away.

Stop use and ask a doctor if irritation or rash occurs. These may be signs of a serious condition.

Keep out of reach of children. If swallowed, get medical help or contact a Poison Control Center right away.

Dosage & Administration

Place enough product on hands to cover all surfaces. Rub hands together until dry.
Supervise children under 6 years of age when using this product to avoid swallowing.

Other Information

- Store between 15-30C (59-86F)
- Avoid freezing and excessive heat above 40C (104F)

Inactive Ingredients

glycerin, hydrogen peroxide, purified water USP